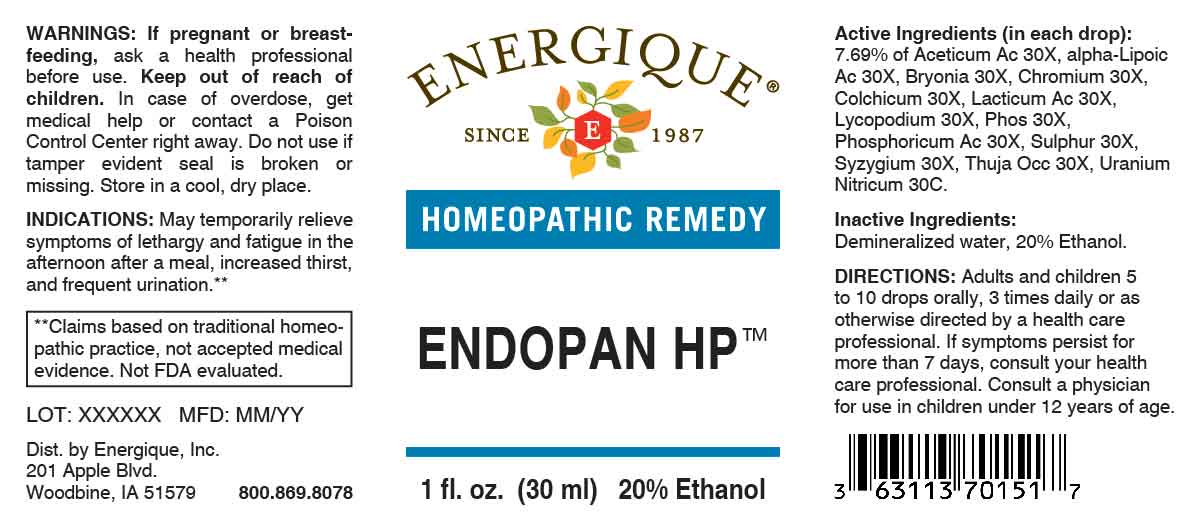 DRUG LABEL: Endopan HP
NDC: 44911-0728 | Form: LIQUID
Manufacturer: Energique, Inc.
Category: homeopathic | Type: HUMAN OTC DRUG LABEL
Date: 20250124

ACTIVE INGREDIENTS: ACETIC ACID 30 [hp_X]/1 mL; ALPHA LIPOIC ACID 30 [hp_X]/1 mL; BRYONIA ALBA ROOT 30 [hp_X]/1 mL; CHROMIUM 30 [hp_X]/1 mL; COLCHICUM AUTUMNALE BULB 30 [hp_X]/1 mL; LACTIC ACID, DL- 30 [hp_X]/1 mL; LYCOPODIUM CLAVATUM SPORE 30 [hp_X]/1 mL; PHOSPHORIC ACID 30 [hp_X]/1 mL; PHOSPHORUS 30 [hp_X]/1 mL; SULFUR 30 [hp_X]/1 mL; SYZYGIUM CUMINI SEED 30 [hp_X]/1 mL; THUJA OCCIDENTALIS LEAFY TWIG 30 [hp_X]/1 mL; URANYL NITRATE HEXAHYDRATE 30 [hp_C]/1 mL
INACTIVE INGREDIENTS: WATER; ALCOHOL

DRUG FACTS:

ACTIVE INGREDIENTS:

(in each drop): 7.69% of Aceticum Acidum 30X, Alpha-Lipoicum Acidum 30X, Bryonia 30X, Chromium 30X, Colchicum Autumnale 30X, Lacticum Acidum 30X, Lycopodium Clavatum 30X, Phosphoricum Acidum 30X, Phosphorus 30X, Sulphur 30X, Syzygium Jambolanum 30X, Thuja Occidentalis 30X, Uranium Nitricum 30C.

PURPOSE:

May temporarily relieve symptoms of lethargy and fatigue in the afternoon after a meal, increased thirst, and frequent urination.**

**Claims based on traditional homeopathic practice, not accepted medical evidence. Not FDA evaluated.

WARNINGS:

If pregnant or breast-feeding, ask a health professional before use.

Keep out of reach of children. In case of overdose, get medical help or contact a Poison Control Center right away.

Do not use if tamper evident seal is broken or missing. Store in a cool, dry place.

DIRECTIONS:

Adults and children 5 to 10 drops orally, 3 times daily or as otherwise directed by a health care professional. If symptoms persist for more than 7 days, consult your health care professional. Consult a physician for use in children under 12 years of age.

INACTIVE INGREDIENTS:

Demineralized water, 20% Ethanol.

KEEP OUT OF REACH OF CHILDREN:

In case of overdose, get medical help or contact a Poison Control Center right away.

INDICATIONS:

May temporarily relieve symptoms of lethargy and fatigue in the afternoon after a meal, increased thirst, and frequent urination.**

**Claims based on traditional homeopathic practice, not accepted medical evidence. Not FDA evaluated.

QUESTIONS:

Dist. by Energique, Inc.

201 Apple Blvd.

Woodbine, IA 51579

800-869-8078

PACKAGE LABEL DISPLAY:

ENERGIQUE

SINCE 1987

HOMEOPATHIC REMEDY

ENDOPAN HP

1 fl. oz. (30 ml)